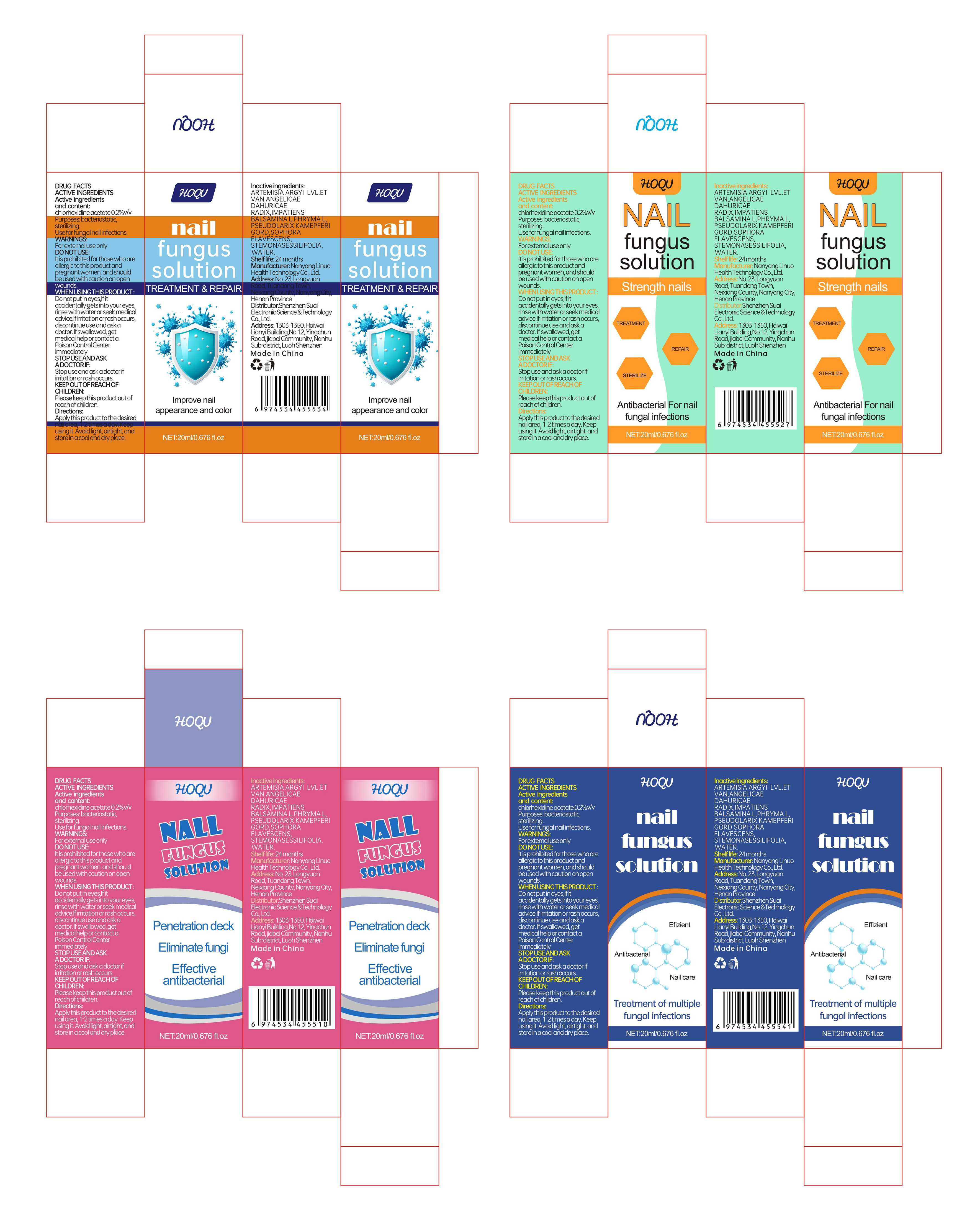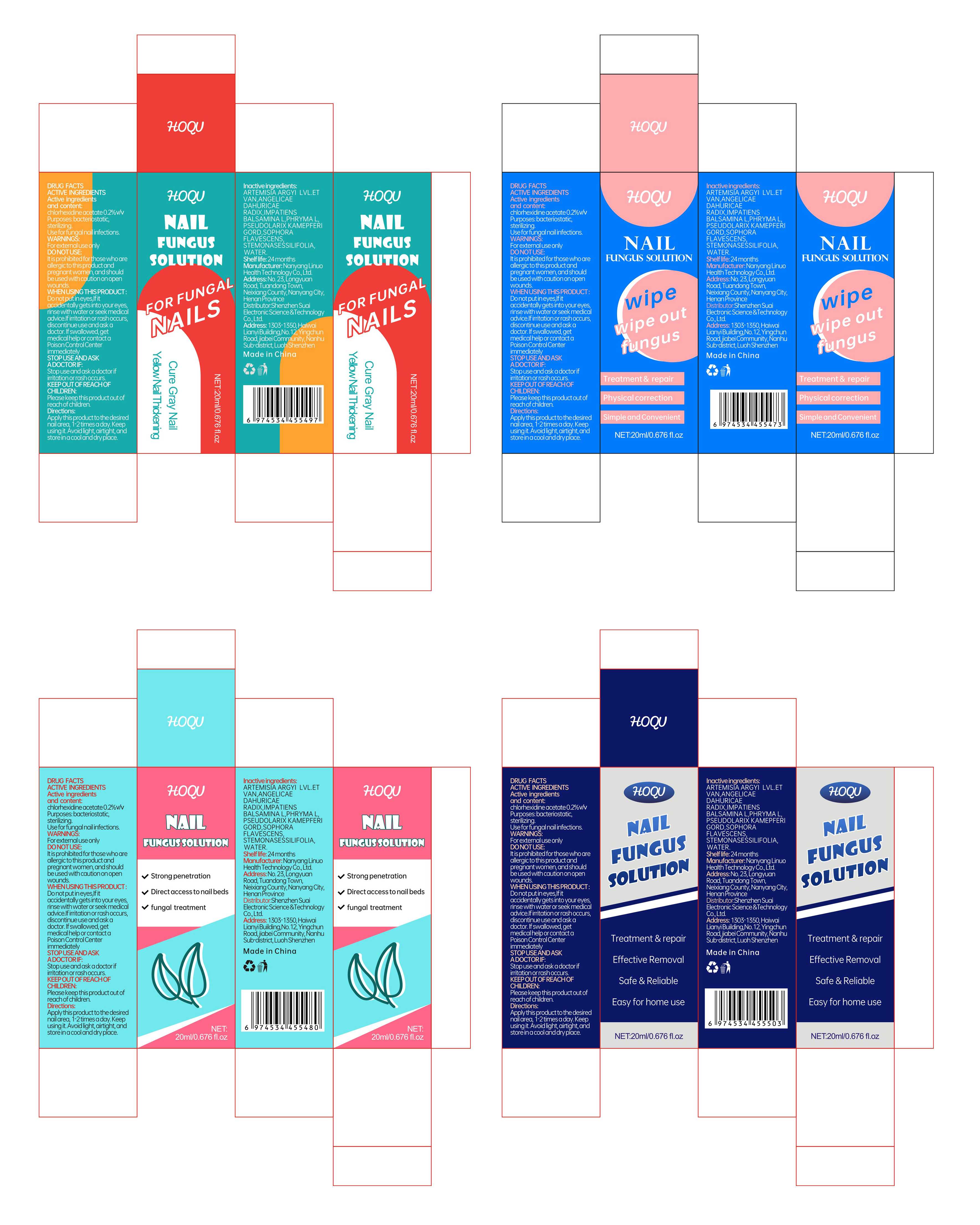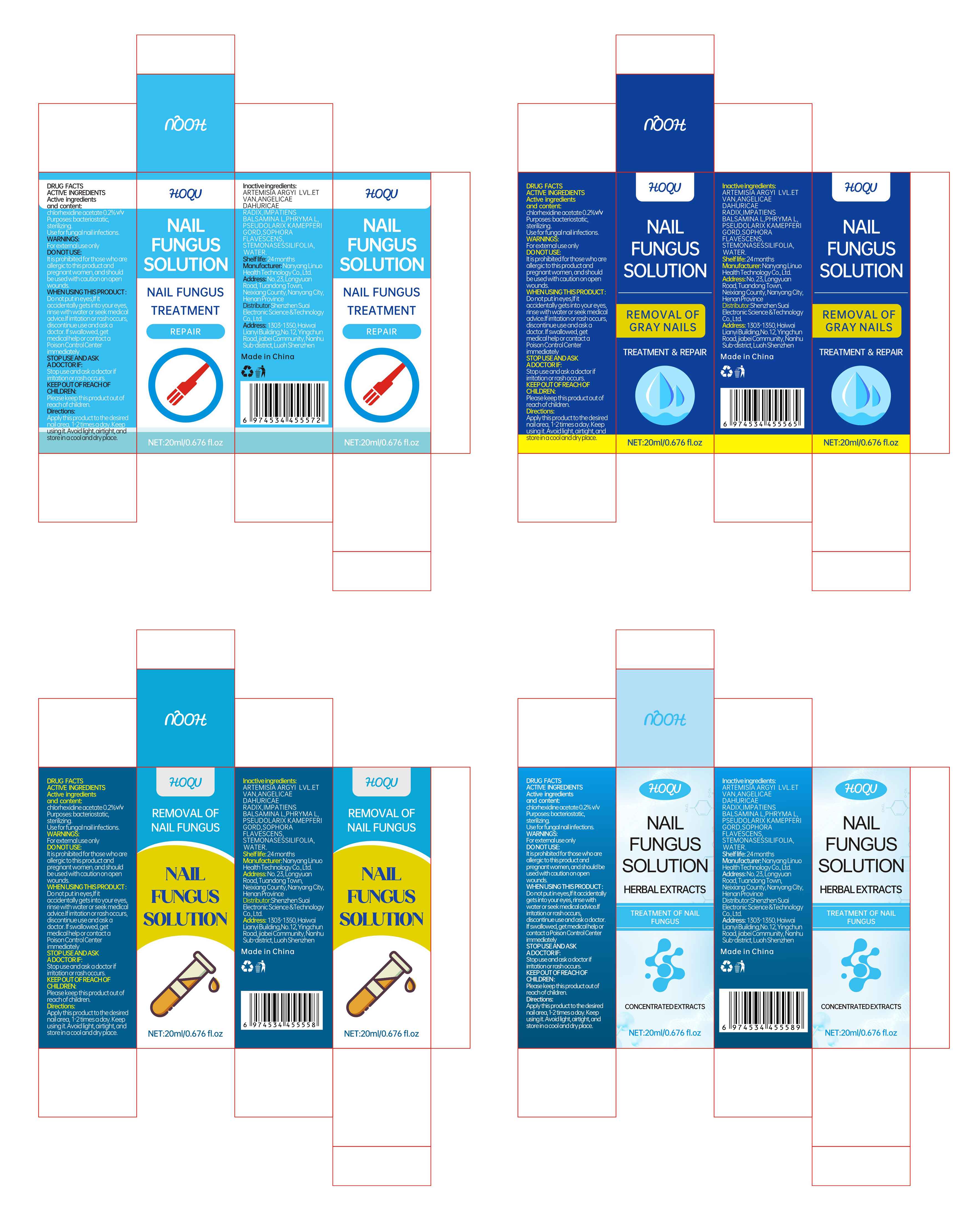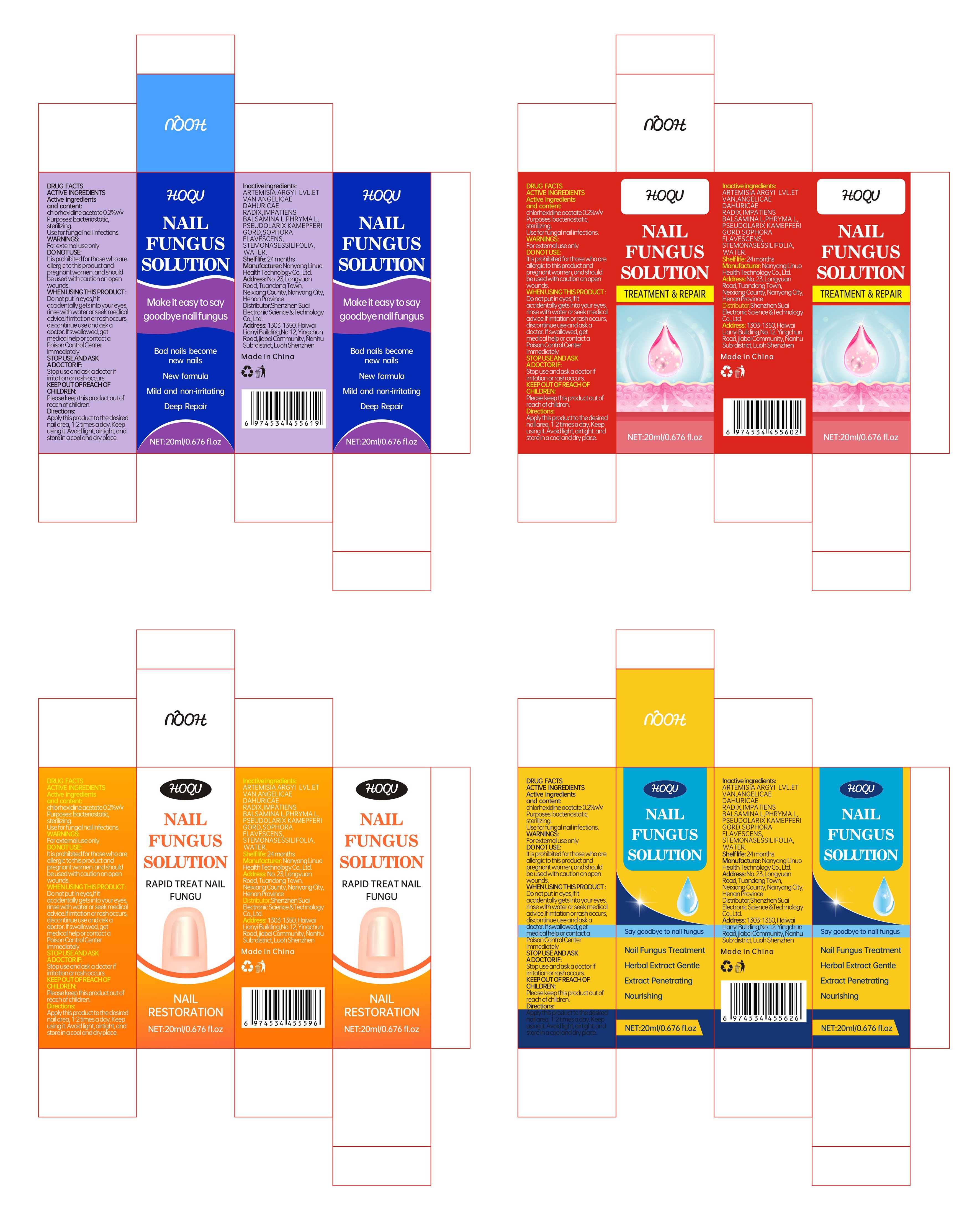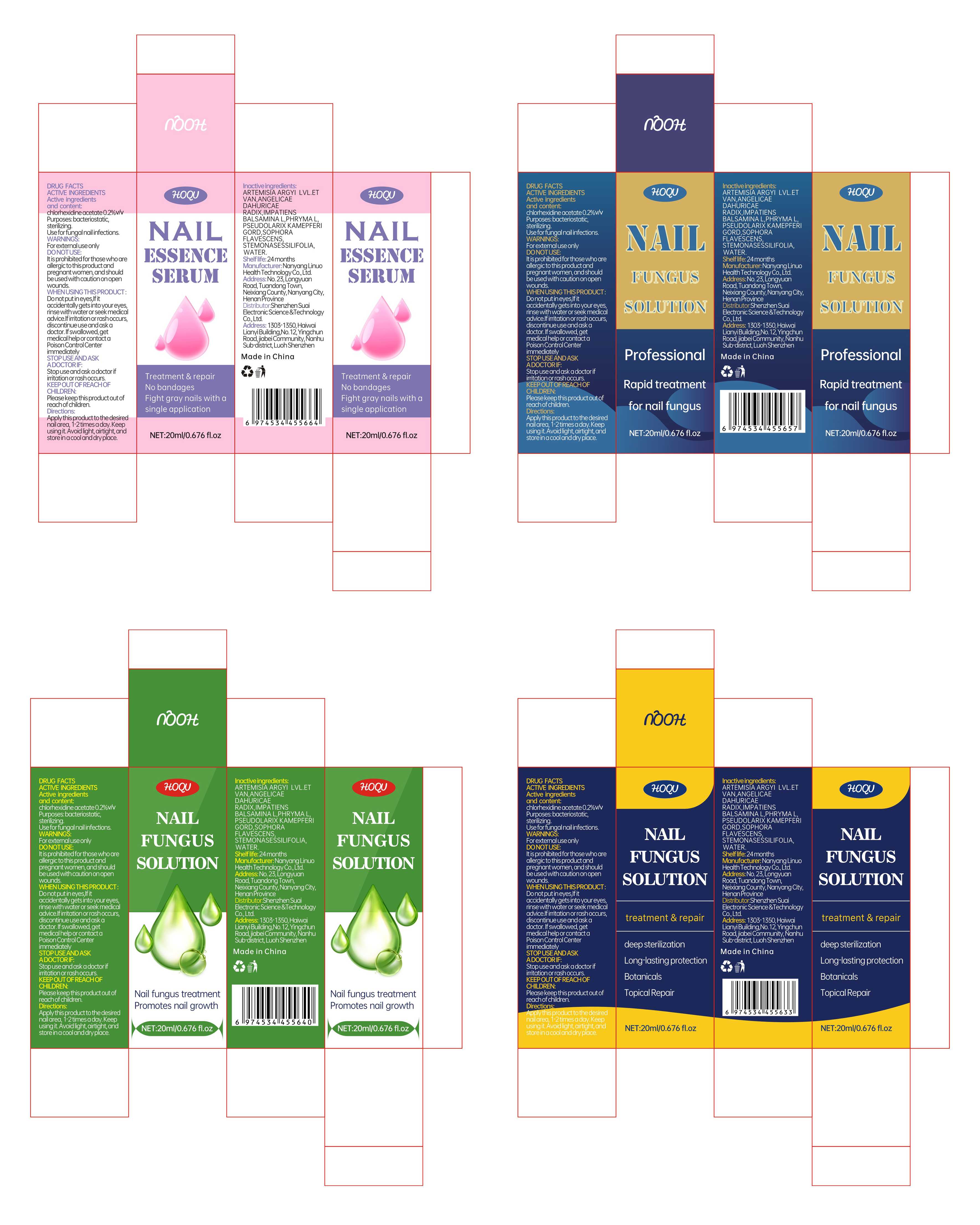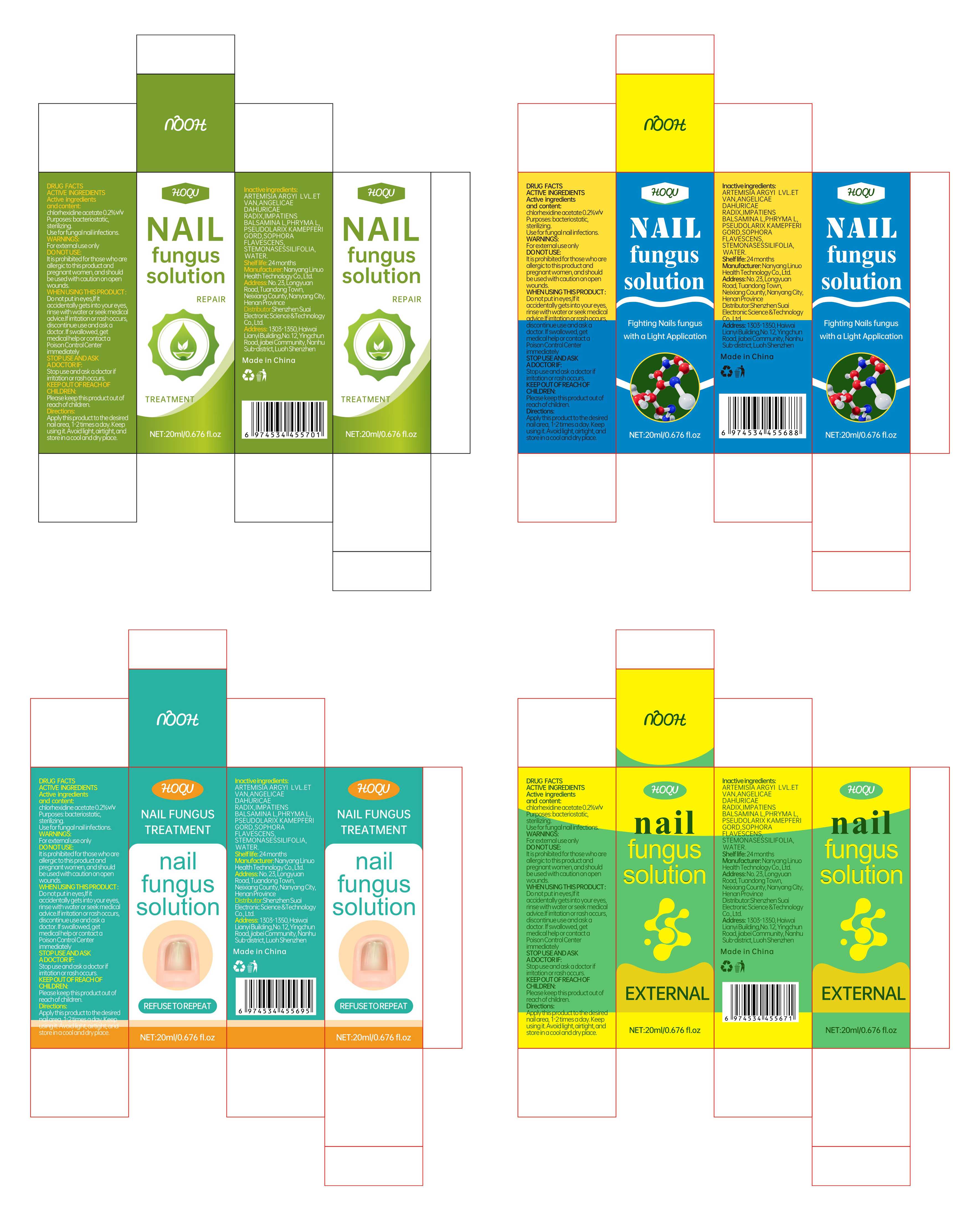 DRUG LABEL: Hoqu Nail Fungus Solution
NDC: 84095-004 | Form: LIQUID
Manufacturer: Shenzhen Suai Electronic Science & Technology Co., Ltd.
Category: otc | Type: HUMAN OTC DRUG LABEL
Date: 20240508

ACTIVE INGREDIENTS: CHLORHEXIDINE ACETATE 0.2 g/100 mL
INACTIVE INGREDIENTS: WATER; ARTEMISIA ARGYI LEAF; SOPHORA FLAVESCENS WHOLE; 3-METHYL-5-HEPTANONE OXIME; PSEUDOLARIX AMABILIS WHOLE; ANGELICA DAHURICA ROOT; IMPATIENS BALSAMINA LEAF; PHRYMA LEPTOSTACHYA WHOLE

84095-004 Update Manufacturer

Active Ingredient

chlorhexidine acetate 0.2% v/v

Purpose

bacteriostatic, sterilizing.

Use

Use for fungal nail infections.

Warnings

For external use only

Do not use

It is prohibited for those who are allergic to this product and pregnant women, and should be used with caution on open wounds.

When Using

Do not put in eyes,If it accidentally gets into your eyes, rinse with water or seek medical advice.If irritation or rash occurs, discontinue use and ask a doctor. If swallowed, get medical help or contact a Poison Control Center immediately

Stop Use

Stop use and ask a doctor if irritation or rash occurs.

Ask Doctor

Do not put in eyes,lf it accidentally gets into your eyes, rinse with water or seek medical advice.lf irritation or rash occurs, discontinue use and ask a doctor. if swallowed, get medical help or contact a Poison Control Center immediately

Keep Oot Of Reach Of Children

Please keep this product out of reach of children.

Directions

Apply this product to the desired nail area, 1-2 times a day. Keep using it. Avoid light, airtight, and store in a cool and dry place.

Inactive ingredients

ARTEMISIA ARGYI LVL.ET VAN,ANGELICAE DAHURICAE RADIX,IMPATIENS BALSAMINA L,PHRYMA L,PSEUDOLARIX KAMEPFERI GORD,SOPHORA FLAVESCENS,STEMONASESSILIFOLIA,WATER.